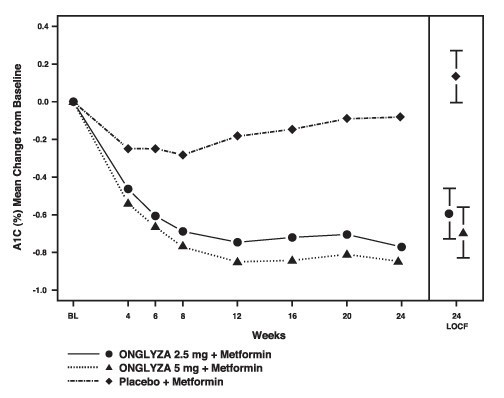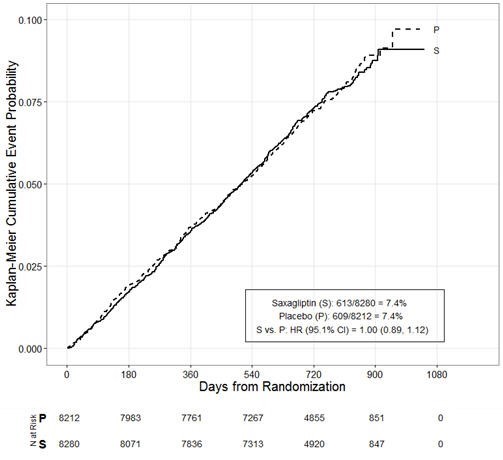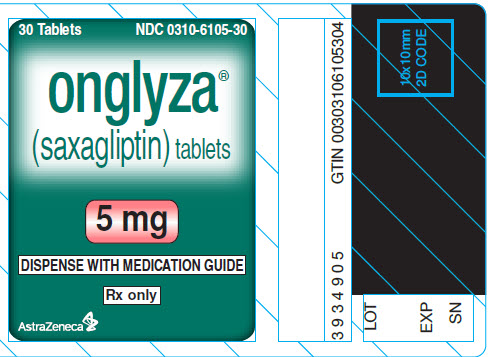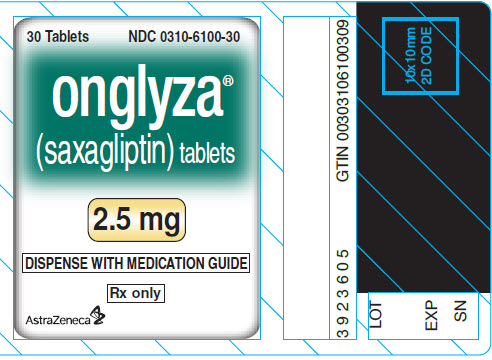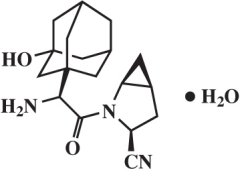 DRUG LABEL: ONGLYZA
NDC: 0310-6105 | Form: TABLET, FILM COATED
Manufacturer: AstraZeneca Pharmaceuticals LP
Category: prescription | Type: HUMAN PRESCRIPTION DRUG LABEL
Date: 20251222

ACTIVE INGREDIENTS: saxagliptin hydrochloride 5 mg/1 1
INACTIVE INGREDIENTS: lactose monohydrate; MICROCRYSTALLINE CELLULOSE; croscarmellose sodium; magnesium stearate

HIGHLIGHTS OF PRESCRIBING INFORMATION

These highlights do not include all the information needed to use ONGLYZA safely and effectively. See full prescribing information for ONGLYZA.
ONGLYZA® (saxagliptin) tablets, for oral use
Initial U.S. Approval: 2009

1 INDICATIONS AND USAGE

ONGLYZA is a dipeptidyl peptidase-4 (DPP-4) inhibitor indicated as an adjunct to diet and exercise to improve glycemic control in adults with type 2 diabetes mellitus. (1.1)

Limitations of use:

- Not recommended for the treatment of type 1 diabetes mellitus or diabetic ketoacidosis. (1.2)

2 DOSAGE AND ADMINISTRATION

- Recommended dosage is 2.5 mg or 5 mg orally once daily taken regardless of meals. (2.1)
- Patients with an eGFR <45 mL/min/1.73 m2 (moderate or severe renal impairment, or end-stage renal disease): Recommended dosage is 2.5 mg once daily regardless of meals. (2.2)
- Assess renal function before starting ONGLYZA and periodically thereafter. (2.2)
- Limit the dosage of ONGLYZA to 2.5 mg daily for patients also taking strong cytochrome P450 3A4/5 (CYP3A4/5) inhibitors (e.g., ketoconazole). (2.3)

3 DOSAGE FORMS AND STRENGTHS

- Tablets: 5 mg and 2.5 mg. (3)

4 CONTRAINDICATIONS

- History of a serious hypersensitivity reaction (e.g., anaphylaxis, angioedema, exfoliative skin conditions) to saxagliptin or any of the ingredients in ONGLYZA. (4)

5 WARNINGS AND PRECAUTIONS

- Pancreatitis: There have been postmarketing reports of acute pancreatitis. If pancreatitis is suspected, promptly discontinue ONGLYZA. (5.1)
- Heart Failure: Consider the risks and benefits of ONGLYZA in patients who have known risk factors for heart failure. Monitor patients for signs and symptoms. (5.2)
- Hypoglycemia with Concomitant Use of Insulin or Insulin Secretagogues: Consider a lower dosage of insulin or insulin secretagogue when used in combination wtih ONGLYZA. (5.3)
- Hypersensitivity-Related Events There have been postmarketing reports of serious hypersensitivity reactions such as anaphylaxis, angioedema, and exfoliative skin conditions. If hypersensitivity reactions occur, discontinue ONGLYZA, treat promptly, and monitor until signs and symptoms resolve. (5.4)
- Arthralgia: Severe and disabling arthralgia has been reported in patients taking DPP-4 inhibitors. Consider as a possible cause for severe joint pain and discontinue drug if appropriate. (5.5)
- Bullous Pemphigoid: There have been postmarketing reports of bullous pemphigoid requiring hospitalization in patients taking DPP-4 inhibitors. Tell patients to report development of blisters or erosions. If bullous pemphigoid is suspected, discontinue ONGLYZA. (5.6)

6 ADVERSE REACTIONS

- Most common adverse reactions (incidence ≥5% and more often than placebo) are upper respiratory tract infection, urinary tract infection, and headache. (6.1)
- Peripheral edema was reported more commonly in patients treated with the combination of ONGLYZA and a thiazolidinedione (TZD) than in patients treated with the combination of placebo and TZD. (6.1)

To report SUSPECTED ADVERSE REACTIONS, contact AstraZeneca at 1-800-236-9933 or FDA at 1-800-FDA-1088 or www.fda.gov/medwatch.

7 DRUG INTERACTIONS

- Strong CYP3A4/5 inhibitors (e.g., ketoconazole): Coadministration with ONGLYZA significantly increases saxagliptin concentrations. Limit ONGLYZA dosage to 2.5 mg once daily when coadministered with a strong CYP3A4/5 inhibitor. (7.1)

FULL PRESCRIBING INFORMATION

1 INDICATIONS AND USAGE

1.1 Monotherapy and Combination Therapy

ONGLYZA is indicated as an adjunct to diet and exercise to improve glycemic control in adults with type 2 diabetes mellitus [see Clinical Studies (14)].

1.2 Limitations of Use

ONGLYZA is not recommended for the treatment of type 1 diabetes mellitus or diabetic ketoacidosis.

2 DOSAGE AND ADMINISTRATION

2.1 Recommended Dosage

The recommended dosage of ONGLYZA is 2.5 mg or 5 mg orally once daily taken regardless of meals. Do not cut, crush, or chew ONGLYZA tablets.

If a dose is missed, advise patients not to take an extra dose. Resume treatment with the next dose.

2.2 Dosage in Patients with Renal Impairment

Assess renal function prior to initiation of ONGLYZA and then as clinically indicated [see Use in Specific Populations (8.6)].

The recommended dosage of ONGLYZA in patients with an eGFR greater than or equal to 45 mL/minute/1.73 m^2 is the same as the recommended dosage in patients with normal renal function [see Dosage and Administration (2.1)].

The dosage of ONGLYZA is 2.5 mg orally once daily for patients with eGFR <45 mL/min/1.73 m^2 [which includes a subset of moderate or severe renal impairment, or with end-stage renal disease (ESRD) requiring hemodialysis] [see Clinical Pharmacology (12.3) and Clinical Studies (14.2)]. ONGLYZA should be administered following hemodialysis. ONGLYZA has not been studied in patients undergoing peritoneal dialysis.

2.3 Dosage Modification with Concomitant Use of Strong CYP3A4/5 Inhibitors

The dosage of ONGLYZA is 2.5 mg orally once daily when used concomitantly with strong cytochrome P450 3A4/5 (CYP3A4/5) inhibitors (e.g., ketoconazole, atazanavir, clarithromycin, indinavir, itraconazole, nefazodone, nelfinavir, ritonavir, saquinavir, and telithromycin) [see Drug Interactions (7.1) and Clinical Pharmacology (12.3)].

3 DOSAGE FORMS AND STRENGTHS

Tablets:

- 5 mg: pink, biconvex, round, film-coated tablets with “5” printed on one side and “4215” printed on the reverse side, in blue ink.
- 2.5 mg: pale yellow to light yellow, biconvex, round, film-coated tablets with “2.5” printed on one side and “4214” printed on the reverse side, in blue ink.

4 CONTRAINDICATIONS

ONGLYZA is contraindicated in patients with a history of a serious hypersensitivity reaction to saxagliptin or any of the ingredients in ONGLYZA. Reactions such as anaphylaxis, angioedema, or exfoliative skin conditions have been reported with ONGLYZA [see Warnings and Precautions (5.4) and Adverse Reactions (6.2)].

5 WARNINGS AND PRECAUTIONS

5.1 Pancreatitis

There have been postmarketing reports of acute pancreatitis in patients taking ONGLYZA. In a cardiovascular outcomes trial enrolling participants with established atherosclerotic cardiovascular disease (ASCVD) or multiple risk factors for ASCVD (SAVOR trial), cases of definite acute pancreatitis were confirmed in 17 of 8240 (0.2%) patients receiving ONGLYZA compared to 9 of 8173 (0.1%) receiving placebo. Preexisting risk factors for pancreatitis were identified in 88% (15/17) of those patients receiving ONGLYZA and in 100% (9/9) of those patients receiving placebo.

After initiation of ONGLYZA, observe patients for signs and symptoms of pancreatitis. If pancreatitis is suspected, promptly discontinue ONGLYZA and initiate appropriate management. It is unknown whether patients with a history of pancreatitis are at increased risk for the development of pancreatitis while using ONGLYZA.

5.2 Heart Failure

In a cardiovascular outcomes trial enrolling participants with established ASCVD or multiple risk factors for ASCVD (SAVOR trial), more patients randomized to ONGLYZA (289/8280, 3.5%) were hospitalized for heart failure compared to patients randomized to placebo (228/8212, 2.8%). In a time-to-first-event analysis the risk of hospitalization for heart failure was higher in the ONGLYZA group (estimated Hazard Ratio: 1.27; 95% CI: 1.07, 1.51). Patients with a prior history of heart failure and patients with renal impairment had a higher risk for hospitalization for heart failure, irrespective of treatment assignment.

Consider the risks and benefits of ONGLYZA prior to initiating treatment in patients at a higher risk for heart failure. Observe patients for signs and symptoms of heart failure during therapy. Advise patients of the characteristic symptoms of heart failure and to immediately report such symptoms. If heart failure develops, evaluate and manage according to current standards of care and consider discontinuation of ONGLYZA.

5.3 Hypoglycemia with Concomitant Use of Insulin or Insulin Secretagogues

When ONGLYZA was used in combination with insulin or an insulin secretagogue, the incidence of confirmed hypoglycemia was increased over that of placebo used in combination with insulin or an insulin secretagogue [see Adverse Reactions (6.1)]. Therefore, a lower dosage of insulin or an insulin secretagogue may be required to reduce the risk of hypoglycemia when used in combination with ONGLYZA [see Drug Interactions (7.2)]. Inform patients using these concomitant medications of the risk of hypoglycemia and educate them on the signs and symptoms of hypoglycemia.

5.4 Hypersensitivity Reactions

There have been postmarketing reports of serious hypersensitivity reactions in patients treated with ONGLYZA. These reactions include anaphylaxis, angioedema, and exfoliative skin conditions. Onset of these reactions occurred within the first 3 months after initiation of treatment with ONGLYZA, with some reports occurring after the first dose. If a serious hypersensitivity reaction is suspected, discontinue ONGLYZA, assess for other potential causes for the event, and institute alternative treatment for diabetes [see Adverse Reactions (6.2)].

Use caution in a patient with a history of angioedema to another dipeptidyl peptidase-4 (DPP-4) inhibitor because it is unknown whether such patients will be predisposed to angioedema with ONGLYZA.

5.5 Severe and Disabling Arthralgia

There have been postmarketing reports of severe and disabling arthralgia in patients taking DPP-4 inhibitors. The time to onset of symptoms following initiation of drug therapy varied from one day to years. Patients experienced relief of symptoms upon discontinuation of the medication. A subset of patients experienced a recurrence of symptoms when restarting the same drug or a different DPP-4 inhibitor. Consider DPP-4 inhibitors as a possible cause for severe joint pain and discontinue drug if appropriate.

5.6 Bullous Pemphigoid

Postmarketing cases of bullous pemphigoid requiring hospitalization have been reported with DPP‑4 inhibitor use. In reported cases, patients typically recovered with topical or systemic immunosuppressive treatment and discontinuation of the DPP-4 inhibitor. Tell patients to report development of blisters or erosions while receiving ONGLYZA. If bullous pemphigoid is suspected, ONGLYZA should be discontinued and referral to a dermatologist should be considered for diagnosis and appropriate treatment.

6 ADVERSE REACTIONS

The following serious adverse reactions are described below or elsewhere in the prescribing information:

- Pancreatitis [see Warnings and Precautions (5.1)]
- Heart Failure [see Warnings and Precautions (5.2)]
- Hypoglycemia with Concomitant Use of Insulin or Insulin Secretagogues [see Warnings and Precautions (5.3)]
- Hypersensitivity Reactions [see Warnings and Precautions (5.4)]
- Severe and disabling arthralgia [see Warnings and Precautions (5.5)]
- Bullous pemphigoid [see Warnings and Precautions (5.6)]

6.1 Clinical Trials Experience

Because clinical trials are conducted under widely varying conditions, adverse reaction rates observed in the clinical trials of a drug cannot be directly compared to rates in the clinical trials of another drug and may not reflect the rates observed in practice.

Adverse Reactions in Placebo-Controlled Trials in Adults with Type 2 Diabetes Mellitus

The data in Table 1 are derived from a pool of 5 placebo-controlled clinical trials [see Clinical Studies (14)]. These data shown in the table reflect exposure of 882 patients to ONGLYZA and a mean duration of exposure to ONGLYZA of 21 weeks. The mean age of these patients was 55 years, 1.4 % were 75 years of age or older and 48.4% were male. The population was 67.5% White, 4.6% Black or African American, 17.4% Asian, 10.5% other races and 9.8% were of Hispanic or Latino ethnicity. At baseline the population had type 2 diabetes mellitus for an average of 5.2 years and a mean HbA1c of 8.2%. Baseline estimated renal function was normal or mildly impaired (eGFR≥60 mL/min/1.73 m^2) in 91% of these patients.

Table 1 shows common adverse reactions, excluding hypoglycemia, associated with the use of ONGLYZA. These adverse reactions occurred more commonly on ONGLYZA than on placebo and occurred in at least 5% of patients treated with ONGLYZA.

Table 1: Adverse Reactions in Placebo-Controlled Trials [The 5 placebo-controlled trials include two monotherapy trials and one add-on combination therapy trial with each of the following: metformin hydrochloride (HCl), thiazolidinedione, or glyburide. Table shows 24-week data regardless of glycemic rescue.] Reported in ≥5% of Patients Treated with ONGLYZA 5 mg and More Commonly than in Patients Treated with Placebo
 | % of Patients
 | ONGLYZA 5 mg N=882 | Placebo N=799
Upper respiratory tract infection | 7.7 | 7.6
Urinary tract infection | 6.8 | 6.1
Headache | 6.5 | 5.9

In patients treated with ONGLYZA 2.5 mg, headache (6.5%) was the only adverse reaction reported at a rate ≥5% and more commonly than in patients treated with placebo.

In the add-on to TZD trial, the incidence of peripheral edema was higher for ONGLYZA 5 mg versus placebo (8.1% and 4.3%, respectively). The incidence of peripheral edema for ONGLYZA 2.5 mg was 3.1%. None of the reported adverse reactions of peripheral edema resulted in trial drug discontinuation. Rates of peripheral edema for ONGLYZA 2.5 mg and ONGLYZA 5 mg versus placebo were 3.6% and 2% versus 3% given as monotherapy, 2.1% and 2.1% versus 2.2% given as add-on therapy to metformin HCl, and 2.4% and 1.2% versus 2.2% given as add-on therapy to glyburide.

The incidence rate of fractures was 1.0 and 0.6 per 100 patient-years, respectively, for ONGLYZA (pooled analysis of 2.5 mg, 5 mg, and 10 mg) and placebo. The 10 mg dosage is not an approved dosage. The incidence rate of fracture events in patients who received ONGLYZA did not increase over time. Causality has not been established and nonclinical studies have not demonstrated adverse effects of ONGLYZA on bone.

An event of thrombocytopenia, consistent with a diagnosis of idiopathic thrombocytopenic purpura, was observed in the clinical program. The relationship of this event to ONGLYZA is not known.

Discontinuation of therapy due to adverse reactions occurred in 2.2%, 3.3%, and 1.8% of patients receiving ONGLYZA 2.5 mg, ONGLYZA 5 mg, and placebo, respectively. The most common adverse reactions (reported in at least 2 patients treated with ONGLYZA 2.5 mg or at least 2 patients treated with ONGLYZA 5 mg) associated with premature discontinuation of therapy included lymphopenia (0.1% and 0.5% versus 0%, respectively), rash (0.2% and 0.3% versus 0.3%), blood creatinine increased (0.3% and 0% versus 0%), and blood creatine phosphokinase increased (0.1% and 0.2% versus 0%).

Adverse Reactions with Concomitant Use with Insulin

In the add-on to insulin trial [see Clinical Studies (14.1)], the incidence of adverse reactions, including serious adverse reactions and discontinuations due to adverse reactions, was similar between ONGLYZA and placebo, except for confirmed hypoglycemia [see Adverse Reactions (6.1)].

Hypoglycemia

Adverse reactions of hypoglycemia were based on all reports of hypoglycemia. A concurrent glucose measurement was not required or was normal in some patients. Therefore, it is not possible to conclusively determine that all these reports reflect true hypoglycemia.

In the add-on to glyburide trial, the overall incidence of reported hypoglycemia was higher for ONGLYZA 2.5 mg and ONGLYZA 5 mg (13.3% and 14.6%) versus placebo (10.1%). The incidence of confirmed hypoglycemia in this trial, defined as symptoms of hypoglycemia accompanied by a fingerstick glucose value of ≤50 mg/dL, was 2.4% and 0.8% for ONGLYZA 2.5 mg and ONGLYZA 5 mg and 0.7% for placebo [see Warnings and Precautions (5.3)]. The incidence of reported hypoglycemia for ONGLYZA 2.5 mg and ONGLYZA 5 mg versus placebo given as monotherapy was 4% and 5.6% versus 4.1%, respectively, 7.8% and 5.8% versus 5% given as add-on therapy to metformin HCl, and 4.1% and 2.7% versus 3.8% given as add-on therapy to TZD. The incidence of reported hypoglycemia was 3.4% in treatment-naive patients given ONGLYZA 5 mg plus metformin HCl and 4% in patients given metformin HCl alone.

In the active-controlled trial comparing add-on therapy with ONGLYZA 5 mg to glipizide in patients inadequately controlled on metformin HCl alone, the incidence of reported hypoglycemia was 3% (19 events in 13 patients) with ONGLYZA 5 mg versus 36.3% (750 events in 156 patients) with glipizide. Confirmed symptomatic hypoglycemia (accompanying fingerstick blood glucose ≤50 mg/dL) was reported in none of the ONGLYZA-treated patients and in 35 glipizide-treated patients (8.1%) (p<0.0001).

In the add-on to insulin trial, the overall incidence of reported hypoglycemia was 18.4% for ONGLYZA 5 mg and 19.9% for placebo. However, the incidence of confirmed symptomatic hypoglycemia (accompanying fingerstick blood glucose ≤50 mg/dL) was higher with ONGLYZA 5 mg (5.3%) versus placebo (3.3%).

In the add-on to metformin HCl plus sulfonylurea trial, the overall incidence of reported hypoglycemia was 10.1% for ONGLYZA 5 mg and 6.3% for placebo. Confirmed hypoglycemia was reported in 1.6% of the ONGLYZA-treated patients and in none of the placebo-treated patients [see Warnings and Precautions (5.3)].

Hypersensitivity Reactions

Hypersensitivity reactions, such as urticaria and facial edema in the 5-trial pooled analysis up to Week 24 were reported in 1.5%, 1.5%, and 0.4% of patients who received ONGLYZA 2.5 mg, ONGLYZA 5 mg, and placebo, respectively. None of these events in patients who received ONGLYZA required hospitalization or were reported as life-threatening by the investigators. One ONGLYZA-treated patient in this pooled analysis discontinued due to generalized urticaria and facial edema.

Renal Impairment

In the SAVOR trial, adverse reactions related to renal impairment, including laboratory changes (i.e., doubling of serum creatinine compared with baseline and serum creatinine >6 mg/dL), were reported in 5.8% (483/8280) of ONGLYZA-treated patients and 5.1% (422/8212) of placebo-treated patients. The most frequently reported adverse reactions included renal impairment (2.1% vs. 1.9%), acute renal failure (1.4% vs. 1.2%), and renal failure (0.8% vs. 0.9%), in the ONGLYZA versus placebo groups, respectively. From baseline to the end of treatment, there was a mean decrease in eGFR of 2.5 mL/min/1.73 m^2 for ONGLYZA-treated patients and a mean decrease of 2.4 mL/min/1.73 m^2 for placebo-treated patients. More patients randomized to ONGLYZA (421/5227, 8.1%) compared to patients randomized to placebo (344/5073, 6.8%) had downward shifts in eGFR from >50 mL/min/1.73 m^2 (i.e., normal or mild renal impairment) to ≤50 mL/min/1.73 m^2 (i.e., moderate or severe renal impairment). The proportions of patients with renal adverse reactions increased with worsening baseline renal function and increased age, regardless of treatment assignment.

Infections

In the unblinded, controlled, clinical trial database for ONGLYZA to date, there have been 6 (0.12%) reports of tuberculosis among the 4959 ONGLYZA-treated patients (1.1 per 1000 patient-years) compared to no reports of tuberculosis among the 2868 comparator-treated patients. Two of these six cases were confirmed with laboratory testing. The remaining cases had limited information or had presumptive diagnoses of tuberculosis. None of the six cases occurred in the United States or in Western Europe. One case occurred in Canada in a patient originally from Indonesia who had recently visited Indonesia. The duration of treatment with ONGLYZA until report of tuberculosis ranged from 144 to 929 days. Post-treatment lymphocyte counts were consistently within the reference range for four cases. One patient had lymphopenia prior to initiation of ONGLYZA that remained stable throughout ONGLYZA treatment. The final patient had an isolated lymphocyte count below normal approximately four months prior to the report of tuberculosis. There have been no spontaneous reports of tuberculosis associated with ONGLYZA use. Causality has not been estimated and there are too few cases to date to determine whether tuberculosis is related to ONGLYZA use.

There has been one case of a potential opportunistic infection in the unblinded, controlled clinical trial database to date in an ONGLYZA-treated patient who developed suspected foodborne fatal salmonella sepsis after approximately 600 days of ONGLYZA therapy. There have been no spontaneous reports of opportunistic infections associated with ONGLYZA use.

Vital Signs

No clinically meaningful changes in vital signs have been observed in patients treated with ONGLYZA.

Laboratory Tests

Absolute Lymphocyte Counts

There was a dose-related mean decrease in absolute lymphocyte count observed with ONGLYZA. From a baseline mean absolute lymphocyte count of approximately 2200 cells/microL, mean decreases of approximately 100 and 120 cells/microL with ONGLYZA 5 mg and 10 mg, respectively, relative to placebo were observed at 24 weeks in a pooled analysis of five placebo-controlled clinical trials. Similar effects were observed when ONGLYZA 5 mg was given in initial combination with metformin HCl compared to metformin HCl alone. There was no difference observed for ONGLYZA 2.5 mg relative to placebo. The proportion of patients who were reported to have a lymphocyte count ≤750 cells/microL was 0.5%, 1.5%, 1.4%, and 0.4% in the ONGLYZA 2.5 mg, 5 mg, 10 mg, and placebo groups, respectively. In most patients, recurrence was not observed with repeated exposure to ONGLYZA although some patients had recurrent decreases upon rechallenge that led to discontinuation of ONGLYZA. The decreases in lymphocyte count were not associated with clinically relevant adverse reactions. The 10 mg dosage is not an approved dosage.

In the SAVOR trial mean decreases of approximately 84 cells/microL with ONGLYZA relative to placebo was observed. The proportion of patients who experienced a decrease in lymphocyte counts to a count of ≤750 cells/microL was 1.6% (136/8280) and 1.0% (78/8212) on ONGLYZA and placebo, respectively.

The clinical significance of this decrease in lymphocyte count relative to placebo is not known. When clinically indicated, such as in settings of unusual or prolonged infection, lymphocyte count should be measured. The effect of ONGLYZA on lymphocyte counts in patients with lymphocyte abnormalities (e.g., human immunodeficiency virus) is unknown.

6.2 Postmarketing Experience

Additional adverse reactions have been identified during post-approval use of ONGLYZA. Because these reactions are reported voluntarily from a population of uncertain size, it is generally not possible to reliably estimate their frequency or establish a causal relationship to drug exposure.

- Gastrointestinal Disorders: Pancreatitis
- Immune System Disorders: Hypersensitivity reactions including anaphylaxis, angioedema, and exfoliative skin conditions
- Musculoskeletal and Connective Tissue Disorders: Rhabdomyolysis, Severe and disabling arthralgia
- Skin and Subcutaneous Tissue Disorders: Bullous pemphigoid

7 DRUG INTERACTIONS

7.1 Strong Inhibitors of CYP3A4/5 Enzymes

Ketoconazole significantly increased saxagliptin exposure. Similar significant increases in plasma concentrations of saxagliptin are anticipated with other strong CYP3A4/5 inhibitors (e.g., atazanavir, clarithromycin, indinavir, itraconazole, nefazodone, nelfinavir, ritonavir, saquinavir, and telithromycin). The dosage of ONGLYZA should be limited to 2.5 mg when coadministered with a strong CYP3A4/5 inhibitor [see Dosage and Administration (2.3) and Clinical Pharmacology (12.3)].

7.2 Insulin or Insulin Secretagogues

Insulin and insulin secretagogues are known to cause hypoglycemia. Concomitant use of ONGLYZA with insulin or an insulin secretagogue may require lower dosages of insulin or the insulin secretagogue to reduce the risk of hypoglycemia [see Warnings and Precautions (5.3)].

8 USE IN SPECIFIC POPULATIONS

8.1 Pregnancy

Risk Summary

Limited data with ONGLYZA in pregnant women are not sufficient to determine a drug-associated risk for major birth defects or miscarriages. There are risks to the mother and fetus associated with poorly controlled diabetes in pregnancy [see Clinical Considerations].

No adverse developmental effects independent of maternal toxicity were observed when saxagliptin was administered to pregnant rats and rabbits during the period of organogenesis and in pregnant and lactating rats during the pre- and postnatal period [see Data].

The estimated background risk of major birth defects is 6 to 10% in women with pre-gestational diabetes with an HbA1c greater than 7 and has been reported to be as high as 20 to 25% in women with an HbA1c greater than 10. The estimated background risk of miscarriage for the indicated population is unknown. In the U.S. general population, the estimated background risk of major birth defects and miscarriage in clinically recognized pregnancies is 2 to 4% and 15 to 20%, respectively.

Clinical Considerations

Disease-associated maternal and/or embryo/fetal risk

Poorly controlled diabetes in pregnancy increases the maternal risk for diabetic ketoacidosis, preeclampsia, spontaneous abortions, preterm delivery, still birth and delivery complications. Poorly controlled diabetes increases the fetal risk for major birth defects, stillbirth, and macrosomia related morbidity.

Data

Animal Data

In embryo-fetal development studies, saxagliptin was administered to pregnant rats and rabbits during the period of organogenesis, corresponding to the first trimester of human pregnancy. No adverse developmental effects were observed

in either species at exposures 1503- and 152-times the 5 mg clinical dose in rats and rabbits, respectively, based on AUC. Saxagliptin crosses the placenta into the fetus following dosing in pregnant rats.

In a prenatal and postnatal development study, no adverse developmental effects were observed in maternal rats administered saxagliptin from gestation day 6 through lactation day 21 at exposures up to 470-times the 5 mg clinical dose, based on AUC.

8.2 Lactation

Risk Summary

There is no information regarding the presence of ONGLYZA in human milk, the effects on the breastfed infant, or the effects on milk production.

Saxagliptin is present in the milk of lactating rats [see Data]. The developmental and health benefits of breastfeeding should be considered along with the mother’s clinical need for ONGLYZA and any potential adverse effects on the breastfed infant from ONGLYZA or from the underlying maternal condition.

Data

Saxagliptin is secreted in the milk of lactating rats at approximately a 1:1 ratio with plasma drug concentrations.

8.4 Pediatric Use

The safety and effectiveness of ONGLYZA as an adjunct to diet and exercise to improve glycemic control in patients with type 2 diabetes mellitus have not been established in pediatric patients.

Effectiveness of ONGLYZA was not demonstrated in a 26-week, placebo-controlled, double-blind randomized clinical trial with a 26-week safety extension (NCT03199053) in 164 pediatric patients aged 10 to 17 years with inadequately controlled type 2 diabetes mellitus.

8.5 Geriatric Use

In the seven, double-blind, controlled clinical safety and efficacy trials of ONGLYZA, a total of 4751 (42.0%) of the 11301 patients randomized to ONGLYZA were 65 years and over, and 1210 (10.7%) were 75 years and over. No overall differences in safety or effectiveness were observed between patients 65 years of age and older and younger adult patients.

Saxagliptin and its active metabolite are eliminated in part by the kidney. Because elderly patients are more likely to have decreased renal function, care should be taken in dose selection in the elderly based on renal function [see Dosage and Administration (2.2) and Clinical Pharmacology (12.3)].

8.6 Renal Impairment

In a 12-week randomized placebo-controlled trial, ONGLYZA 2.5 mg was administered orally to 85 patients with moderate (n=48) or severe (n=18) renal impairment or end-stage renal disease (ESRD) (n=19) [see Clinical Studies (14)]. The incidence of adverse events, including serious adverse events and discontinuations due to adverse events, was similar between ONGLYZA and placebo. The overall incidence of reported hypoglycemia was 20% among patients treated with ONGLYZA 2.5 mg and 22% among patients treated with placebo. Four ONGLYZA-treated patients (4.7%) and three placebo-treated patients (3.5%) reported at least one episode of confirmed symptomatic hypoglycemia (accompanying fingerstick glucose ≤50 mg/dL).

10 OVERDOSAGE

In a controlled clinical trial, once-daily, orally-administered ONGLYZA in healthy patients at doses up to 400 mg daily for 2 weeks (80-times the MRHD) had no dose-related clinical adverse reactions and no clinically meaningful effect on QTc interval or heart rate.

In the event of an overdose, initiate appropriate supportive treatment as dictated by the patient’s clinical status. Saxagliptin and its active metabolite are removed by hemodialysis (23% of dose over 4 hours). Contact the Poison Help Line, (1-800-222-1222) or a medical toxicologist for additional overdosage management recommendations.

11 DESCRIPTION

Saxagliptin is an orally-active inhibitor of the DPP-4 enzyme.

Saxagliptin monohydrate is described chemically as (1S,3S,5S)-2-[(2S)-2-Amino-2-(3-hydroxytricyclo[3.3.1.1^3,7]dec-1-yl)acetyl]-2-azabicyclo[3.1.0]hexane-3-carbonitrile, monohydrate or (1S,3S,5S)-2-[(2S)-2-Amino-2-(3-hydroxyadamantan-1-yl)acetyl]-2-azabicyclo[3.1.0]hexane-3-carbonitrile hydrate. The empirical formula is C18H25N3O2•H2O and the molecular weight is 333.43. The structural formula is:

Saxagliptin monohydrate is a white to light yellow or light brown, non-hygroscopic, crystalline powder. It is sparingly soluble in water at 24°C ± 3°C, slightly soluble in ethyl acetate, and soluble in methanol, ethanol, isopropyl alcohol, acetonitrile, acetone, and polyethylene glycol 400 (PEG 400).

Each film-coated tablet of ONGLYZA for oral use contains either 2.79 mg saxagliptin hydrochloride (anhydrous) equivalent to 2.5 mg saxagliptin or 5.58 mg saxagliptin hydrochloride (anhydrous) equivalent to 5 mg saxagliptin and the following inactive ingredients: croscarmellose sodium, lactose monohydrate, magnesium stearate and microcrystalline cellulose. In addition, the film coating contains the following inactive ingredients: iron oxides, polyethylene glycol, polyvinyl alcohol, talc, and titanium dioxide.

12 CLINICAL PHARMACOLOGY

12.1 Mechanism of Action

Increased concentrations of the incretin hormones such as glucagon-like peptide-1 (GLP-1) and glucose-dependent insulinotropic polypeptide (GIP) are released into the bloodstream from the small intestine in response to meals. These hormones cause insulin release from the pancreatic beta cells in a glucose-dependent manner but are inactivated by the DPP-4 enzyme within minutes. GLP-1 also lowers glucagon secretion from pancreatic alpha cells, reducing hepatic glucose production. In patients with type 2 diabetes mellitus, concentrations of GLP-1 are reduced but the insulin response to GLP-1 is preserved. Saxagliptin is a competitive DPP-4 inhibitor that slows the inactivation of the incretin hormones, thereby increasing their bloodstream concentrations and reducing fasting and postprandial glucose concentrations in a glucose-dependent manner in patients with type 2 diabetes mellitus.

12.2 Pharmacodynamics

In patients with type 2 diabetes mellitus, administration of ONGLYZA inhibits DPP-4 enzyme activity for a 24-hour period. After an oral glucose load or a meal, this DPP-4 inhibition resulted in a 2- to 3-fold increase in circulating levels of active GLP-1 and GIP, decreased glucagon concentrations, and increased glucose-dependent insulin secretion from pancreatic beta cells. The rise in insulin and decrease in glucagon were associated with lower fasting glucose concentrations and reduced glucose excursion following an oral glucose load or a meal.

Cardiac Electrophysiology

In a randomized, double-blind, placebo-controlled, 4-way crossover, active comparator trial using moxifloxacin in 40 healthy subjects, ONGLYZA was not associated with clinically meaningful prolongation of the QTc interval or heart rate at daily doses up to 40 mg (8-times the MRHD).

12.3 Pharmacokinetics

The pharmacokinetics of saxagliptin and its active metabolite, 5-hydroxy saxagliptin were similar in healthy subjects and in patients with type 2 diabetes mellitus. The Cmax and AUC values of saxagliptin and its active metabolite increased proportionally in the 2.5 to 400 mg dose range. Following a 5 mg single oral dose of saxagliptin to healthy subjects, the mean plasma AUC values for saxagliptin and its active metabolite were 78 ng•h/mL and 214 ng•h/mL, respectively. The corresponding plasma Cmax values were 24 ng/mL and 47 ng/mL, respectively. The average variability (%CV) for AUC and Cmax for both saxagliptin and its active metabolite was less than 25%.

No appreciable accumulation of either saxagliptin or its active metabolite was observed with repeated once-daily dosing at any dose level. No dose- and time-dependence were observed in the clearance of saxagliptin and its active metabolite over 14 days of once-daily dosing with saxagliptin at doses ranging from 2.5 to 400 mg.

Absorption

The median time to maximum concentration (Tmax) following the 5 mg once daily dose was 2 hours for saxagliptin and 4 hours for its active metabolite.

Effect of Food

Administration with a high-fat meal resulted in an increase in Tmax of saxagliptin by approximately 20 minutes as compared to fasted conditions. There was a 27% increase in the AUC of saxagliptin when given with a meal as compared to fasted conditions. ONGLYZA may be administered with or without food.

Distribution

The in vitro protein binding of saxagliptin and its active metabolite in human serum is negligible. Therefore, changes in blood protein levels in various disease states (e.g., renal or hepatic impairment) are not expected to alter the disposition of saxagliptin.

Metabolism

The metabolism of saxagliptin is primarily mediated by cytochrome P450 3A4/5 (CYP3A4/5). The major metabolite of saxagliptin is also a DPP-4 inhibitor, which is one-half as potent as saxagliptin. Therefore, strong CYP3A4/5 inhibitors and inducers will alter the pharmacokinetics of saxagliptin and its active metabolite [see Drug Interactions (7.1)].

Excretion

Saxagliptin is eliminated by both renal and hepatic pathways. Following a single 50 mg dose of ^14C-saxagliptin, 24%, 36%, and 75% of the dose was excreted in the urine as saxagliptin, its active metabolite, and total radioactivity, respectively. The average renal clearance of saxagliptin (~230 mL/min) was greater than the average estimated glomerular filtration rate (~120 mL/min), suggesting some active renal excretion. A total of 22% of the administered radioactivity was recovered in feces representing the fraction of the saxagliptin dose excreted in bile and/or unabsorbed drug from the gastrointestinal tract. Following a single oral dose of ONGLYZA 5 mg to healthy subjects, the mean plasma terminal half-life (t1/2) for saxagliptin and its active metabolite was 2.5 and 3.1 hours, respectively.

Specific Populations

Geriatric Patients

No dosage adjustment is recommended based on age alone. Elderly subjects (65-80 years) had 23% and 59% higher geometric mean Cmax and geometric mean AUC values, respectively, for saxagliptin than young subjects (18-40 years). Differences in active metabolite pharmacokinetics between elderly and young subjects generally reflected the differences observed in saxagliptin pharmacokinetics. The difference between the pharmacokinetics of saxagliptin and the active metabolite in young and elderly subjects is likely due to multiple factors including declining renal function and metabolic capacity with increasing age. Age was not identified as a significant covariate on the apparent clearance of saxagliptin and its active metabolite in the population pharmacokinetic analysis.

Male and Female Patients

No dosage adjustment is recommended based on gender. There were no differences observed in saxagliptin pharmacokinetics between males and females. Compared to males, females had approximately 25% higher exposure values for the active metabolite than males, but this difference is unlikely to be of clinical relevance. Gender was not identified as a significant covariate on the apparent clearance of saxagliptin and its active metabolite in the population pharmacokinetic analysis.

Racial or Ethnic Groups

No dosage adjustment is recommended based on race. The population pharmacokinetic analysis compared the pharmacokinetics of saxagliptin and its active metabolite in 309 White subjects with 105 subjects of other races (consisting of six racial groups). No significant difference in the pharmacokinetics of saxagliptin and its active metabolite were detected between these two populations.

Patients with Renal Impairment

A single-dose, open-label study was conducted to evaluate the pharmacokinetics of saxagliptin (10 mg dose) in subjects with varying degrees of chronic renal impairment compared to subjects with normal renal function. The 10 mg dosage is not an approved dosage.

The degree of renal impairment did not affect Cmax of saxagliptin or its metabolite. In subjects with moderate renal impairment with (eGFR 30 to less than 45 mL/min/1.73 m^2), severe renal impairment (eGFR 15 to less than 30 mL/min/1.73 m^2) and ESRD patient on hemodialysis, the AUC values of saxagliptin or its active metabolite were >2 fold higher than AUC values in subjects with normal renal function.

Patients with Hepatic Impairment

In subjects with hepatic impairment (Child-Pugh classes A, B, and C), mean Cmax and AUC of saxagliptin were up to 8% and 77% higher, respectively, compared to healthy matched controls following administration of a single 10 mg dose of saxagliptin. The 10 mg dosage is not an approved dosage. The corresponding Cmax and AUC of the active metabolite were up to 59% and 33% lower, respectively, compared to healthy matched controls. These differences are not considered to be clinically meaningful.

Body Mass Index

No dosage adjustment is recommended based on body mass index (BMI) which was not identified as a significant covariate on the apparent clearance of saxagliptin or its active metabolite in the population pharmacokinetic analysis.

Drug Interaction Studies

In Vitro Assessment of Drug Interactions

The metabolism of saxagliptin is primarily mediated by CYP3A4/5.

In in vitro studies, saxagliptin and its active metabolite did not inhibit CYP1A2, 2A6, 2B6, 2C9, 2C19, 2D6, 2E1, or 3A4, or induce CYP1A2, 2B6, 2C9, or 3A4. Therefore, saxagliptin is not expected to alter the metabolic clearance of coadministered drugs that are metabolized by these enzymes. Saxagliptin is a P-glycoprotein (P-gp) substrate but is not a significant inhibitor or inducer of P-gp.

In Vivo Assessment of Drug Interactions

Table 2: Effect of Coadministered Drugs on Systemic Exposures of Saxagliptin and its Active Metabolite, 5-hydroxy Saxagliptin
Coadministered Drug | Dosage of Coadministered Drug [Single dose unless otherwise noted. The 10 mg saxagliptin dose is not an approved dosage.] | Dosage of Saxagliptin | Geometric Mean Ratio (ratio with/without coadministered drug) No Effect = 1.00
 |  |  |  | AUC [AUC = AUC(INF) for drugs given as single dose and AUC = AUC(TAU) for drugs given in multiple doses.] | Cmax
No dosing adjustments required for the following:
Metformin | 1,000 mg | 100 mg | saxagliptin 5-hydroxy saxagliptin | 0.98 0.99 | 0.79 0.88
Glyburide | 5 mg | 10 mg | saxagliptin 5-hydroxy saxagliptin | 0.98 ND | 1.08 ND
Dapagliflozin | 10 mg single dose | 5 mg single dose | saxagliptin; 5-hydroxy saxagliptin | ↓1%; ↑9% | ↓7%; ↑6%
Pioglitazone [Results exclude one subject.] | 45 mg QD for 10 days | 10 mg QD for 5 days | saxagliptin 5-hydroxy saxagliptin | 1.11 ND | 1.11 ND
Digoxin | 0.25 mg q6h first day followed by q12h second day followed by QD for 5 days | 10 mg QD for 7 days | saxagliptin 5-hydroxy saxagliptin | 1.05 1.06 | 0.99 1.02
Simvastatin | 40 mg QD for 8 days | 10 mg QD for 4 days | saxagliptin 5-hydroxy saxagliptin | 1.12 1.02 | 1.21 1.08
Diltiazem | 360 mg LA QD for 9 days | 10 mg | saxagliptin 5-hydroxy saxagliptin | 2.09 0.66 | 1.63 0.57
Rifampin [The plasma DPP4 activity inhibition over a 24-hour dose interval was not affected by rifampin.] | 600 mg QD for 6 days | 5 mg | saxagliptin 5-hydroxy saxagliptin | 0.24 1.03 | 0.47 1.39
Omeprazole | 40 mg QD for 5 days | 10 mg | saxagliptin 5-hydroxy saxagliptin | 1.13 ND | 0.98 ND
Aluminum hydroxide + magnesium hydroxide + simethicone | aluminum hydroxide: 2400 mg magnesium hydroxide: 2400 mg simethicone: 240 mg | 10 mg | saxagliptin 5-hydroxy saxagliptin | 0.97 ND | 0.74 ND
Famotidine | 40 mg | 10 mg | saxagliptin 5-hydroxy saxagliptin | 1.03 ND | 1.14 ND
Limit ONGLYZA dose to 2.5 mg once daily when coadministered with strong CYP3A4/5 inhibitors [see Drug Interactions (7.1) and Dosage and Administration (2.3)]:
Ketoconazole | 200 mg BID for 9 days | 100 mg | saxagliptin 5-hydroxy saxagliptin | 2.45 0.12 | 1.62 0.05
Ketoconazole | 200 mg BID for 7 days | 20 mg | saxagliptin 5-hydroxy saxagliptin | 3.67 ND | 2.44 ND

ND=not determined; QD=once daily; q6h=every 6 hours; q12h=every 12 hours; BID=twice daily; LA=long acting

Table 3: Effect of Saxagliptin on Systemic Exposures of Coadministered Drugs
Coadministered Drug | Dosage of Coadministered Drug [Single dose unless otherwise noted. The 10 mg and 100 mg saxagliptin doses are not approved dosages.] | Dosage of Saxagliptin | Geometric Mean Ratio (ratio with/without saxagliptin) No Effect = 1.00
Coadministered Drug | Dosage of Coadministered Drug [Single dose unless otherwise noted. The 10 mg and 100 mg saxagliptin doses are not approved dosages.] | Dosage of Saxagliptin |  | AUC [AUC = AUC(INF) for drugs given as single dose and AUC = AUC(TAU) for drugs given in multiple doses.] | Cmax
No dosing adjustments required for the following:
Metformin | 1,000 mg | 100 mg | metformin | 1.20 | 1.09
Glyburide | 5 mg | 10 mg | glyburide | 1.06 | 1.16
Pioglitazone [Results include all subjects.] | 45 mg QD for 10 days | 10 mg QD for 5 days | pioglitazone hydroxy-pioglitazone | 1.08 ND | 1.14 ND
Digoxin | 0.25 mg q6h first day followed by q12h second day followed by QD for 5 days | 10 mg QD for 7 days | digoxin | 1.06 | 1.09
Simvastatin | 40 mg QD for 8 days | 10 mg QD for 4 days | simvastatin simvastatin acid | 1.04 1.16 | 0.88 1.00
Diltiazem | 360 mg LA QD for 9 days | 10 mg | diltiazem | 1.10 | 1.16
Ketoconazole | 200 mg BID for 9 days | 100 mg | ketoconazole | 0.87 | 0.84
Ethinyl estradiol and Norgestimate | ethinyl estradiol 0.035 mg and norgestimate 0.250 mg for 21 days | 5 mg QD for 21 days | ethinyl estradiol norelgestromin norgestrel | 1.07 1.10 1.13 | 0.98 1.09 1.17

ND=not determined; QD=once daily; q6h=every 6 hours; q12h=every 12 hours; BID=twice daily; LA=long acting

13 NONCLINICAL TOXICOLOGY

13.1 Carcinogenesis, Mutagenesis, Impairment of Fertility

Carcinogenesis

Carcinogenicity was evaluated in 2-year studies conducted in CD-1 mice and Sprague-Dawley rats. Saxagliptin did not increase the incidence of tumors in mice dosed orally at 50, 250, and 600 mg/kg up to 870-times (males) and 1165-times (females) the 5 mg/day clinical dose, based on AUC. Saxagliptin did not increase the incidence of tumors in rats dosed orally at 25, 75, 150, and 300 mg/kg up to 355-times (males) and 2217-times (females) the 5 mg/day clinical dose, based on AUC.

Mutagenesis

Saxagliptin was not mutagenic or clastogenic in a battery of genotoxicity tests (Ames bacterial mutagenesis, human and rat lymphocyte cytogenetics, rat bone marrow micronucleus and DNA repair assays). The active metabolite of saxagliptin was not mutagenic in an Ames bacterial assay.

Impairment of Fertility

Saxagliptin administered to rats had no effect on fertility or the ability to maintain a litter at exposures up to 603-times and 776-times the 5 mg clinical dose in males and females, based on AUC.

13.2 Animal Toxicology and/or Pharmacology

Saxagliptin produced adverse skin changes in the extremities of cynomolgus monkeys (scabs and/or ulceration of tail, digits, scrotum, and/or nose). Skin lesions were reversible within exposure approximately 20-times the 5 mg clinical dose, but in some cases were irreversible and necrotizing at higher exposures. Adverse skin changes were not observed at exposures similar to (1- to 3-times) the 5 mg clinical dose. Clinical correlates to skin lesions in monkeys have not been observed in human clinical trials of saxagliptin.

14 CLINICAL STUDIES

14.1 Glycemic Control Trials in Adults with Type 2 Diabetes Mellitus

ONGLYZA has been studied as monotherapy and in combination with metformin HCl, glyburide, and thiazolidinedione (pioglitazone and rosiglitazone) therapy.

A total of 4148 patients with type 2 diabetes mellitus were randomized in six, double-blind, controlled clinical trials conducted to evaluate the safety and glycemic efficacy of ONGLYZA administered orally. A total of 3021 patients in these trials were treated with ONGLYZA. In these trials, the mean age was 54 years, and 71% of patients were White, 16% were Asian, 4% were Black or African American, and 9% were of other racial groups. An additional 423 patients, including 315 who received ONGLYZA, participated in a placebo-controlled, dose-ranging trial of 6 to 12 weeks in duration.

In these six, double-blind trials, ONGLYZA was evaluated at doses of 2.5 mg and 5 mg once daily. Three of these trials also evaluated an ONGLYZA dose of 10 mg daily. The 10 mg daily dose of ONGLYZA did not provide greater efficacy than the 5 mg daily dose. The 10 mg dosage is not an approved dosage. Treatment with ONGLYZA 5 mg and 2.5 mg doses produced statistically significant improvements in A1C, fasting plasma glucose (FPG), and 2-hour postprandial glucose (PPG) following a standard oral glucose tolerance test (OGTT), compared to control. Reductions in A1C were seen across subgroups including gender, age, race, and baseline BMI.

ONGLYZA was not associated with significant changes from baseline in body weight or fasting serum lipids compared to placebo.

ONGLYZA has also been evaluated in five additional trials in patients with type 2 diabetes mellitus: an active-controlled trial comparing add-on therapy with ONGLYZA to glipizide in 858 patients inadequately controlled on metformin HCl alone, a trial comparing ONGLYZA to placebo in 455 patients inadequately controlled on insulin alone or on insulin in combination with metformin HCl, a trial comparing ONGLYZA to placebo in 257 patients inadequately controlled on metformin HCl plus a sulfonylurea, a trial comparing ONGLYZA to placebo in 315 patients inadequately controlled on dapagliflozin and metformin HCl, and a trial comparing ONGLYZA to placebo in 170 patients with type 2 diabetes mellitus and moderate or severe renal impairment or ESRD.

Monotherapy

A total of 766 patients with type 2 diabetes mellitus inadequately controlled on diet and exercise (A1C ≥7% to ≤10%) participated in two 24-week, double-blind, placebo-controlled trials evaluating the efficacy and safety of ONGLYZA monotherapy.

In the first trial, following a 2-week single-blind diet, exercise, and placebo lead-in period, 401 patients were randomized to 2.5 mg, 5 mg, or 10 mg of ONGLYZA or placebo. The 10 mg dosage is not an approved dosage. Patients who failed to meet specific glycemic goals during the trial were treated with metformin HCl rescue therapy, added on to placebo or ONGLYZA. Efficacy was evaluated at the last measurement prior to rescue therapy for patients needing rescue. Dose titration of ONGLYZA was not permitted.

Treatment with ONGLYZA 2.5 mg and 5 mg daily provided significant improvements in A1C, FPG, and PPG compared to placebo (Table 4). The percentage of patients who discontinued for lack of glycemic control or who were rescued for meeting prespecified glycemic criteria was 16% in the ONGLYZA 2.5 mg treatment group, 20% in the ONGLYZA 5 mg treatment group, and 26% in the placebo group.

Table 4: Glycemic Parameters at Week 24 in a Placebo-Controlled trial of ONGLYZA Monotherapy in Patients with Type 2 Diabetes Mellitus [Intent-to-treat population using last observation on trial or last observation prior to metformin HCl rescue therapy for patients needing rescue.]
Efficacy Parameter | ONGLYZA 2.5 mg N=102 | ONGLYZA 5 mg N=106 | Placebo N=95
Hemoglobin A1C (%) | N=100 | N=103 | N=92
Baseline (mean) | 7.9 | 8.0 | 7.9
Change from baseline (adjusted mean [Least squares mean adjusted for baseline value.]) | −0.4 | −0.5 | +0.2
Difference from placebo (adjusted mean) | −0.6 [p-value <0.0001 compared to placebo.] | −0.6
95% Confidence Interval | (−0.9, −0.3) | (−0.9, −0.4)
Percent of patients achieving A1C <7% | 35% (35/100) | 38% [p-value <0.05 compared to placebo.] (39/103) | 24% (22/92)
Fasting Plasma Glucose (mg/dL) | N=101 | N=105 | N=92
Baseline (mean) | 178 | 171 | 172
Change from baseline (adjusted mean) | −15 | −9 | +6
Difference from placebo (adjusted mean) | −21 | −15
95% Confidence Interval | (−31, −10) | (−25, −4)
2-hour Postprandial Glucose (mg/dL) | N=78 | N=84 | N=71
Baseline (mean) | 279 | 278 | 283
Change from baseline (adjusted mean) | −45 | −43 | −6
Difference from placebo (adjusted mean) | −39 [Significance was not tested for the 2-hour PPG for the 2.5 mg dose of ONGLYZA.] | −37
95% Confidence Interval | (−61, −16) | (−59, −15)

A second 24-week monotherapy trial was conducted to assess a range of dosing regimens for ONGLYZA.

Treatment-naive patients with inadequately controlled type 2 diabetes mellitus (A1C ≥7% to ≤10%) underwent a 2-week, single-blind diet, exercise, and placebo lead-in period. A total of 365 patients were randomized to 2.5 mg every morning, 5 mg every morning, 2.5 mg with possible titration to 5 mg every morning, or 5 mg every evening of ONGLYZA, or placebo. Patients who failed to meet specific glycemic goals during the trial were treated with metformin HCl rescue therapy added on to placebo or ONGLYZA; the number of patients randomized per treatment group ranged from 71 to 74.

Treatment with either ONGLYZA 5 mg every morning or 5 mg every evening provided significant improvements in A1C versus placebo (mean placebo-corrected reductions of −0.4% and −0.3%, respectively). Treatment with ONGLYZA 2.5 mg every morning also provided significant improvement in A1C versus placebo (mean placebo-corrected reduction of −0.4%).

Combination Therapy

Add-On Combination Therapy with Metformin HCl

A total of 743 patients with type 2 diabetes mellitus participated in this 24-week, randomized, double-blind, placebo-controlled trial to evaluate the efficacy and safety of ONGLYZA in combination with metformin HCl in patients with inadequate glycemic control (A1C ≥7% and ≤10%) on metformin alone. To qualify for enrollment, patients were required to be on a stable dose of metformin HCl (1,500-2,550 mg daily) for at least 8 weeks.

Patients who met eligibility criteria were enrolled in a single-blind, 2-week, dietary and exercise placebo lead-in period during which patients received metformin HCl at their pre-trial dose, up to 2,500 mg daily. Following the lead-in period, eligible patients were randomized to 2.5 mg, 5 mg, or 10 mg of ONGLYZA or placebo in addition to their current dose of open-label metformin HCl. The 10 mg dosage of ONGLYZA is not an approved dosage. Patients who failed to meet specific glycemic goals during the trial were treated with pioglitazone rescue therapy, added on to existing trial medications. Dose titrations of ONGLYZA and metformin HCl were not permitted.

ONGLYZA 2.5 mg and 5 mg add-on to metformin provided significant improvements in A1C, FPG, and PPG compared with placebo add-on to metformin (Table 5). Mean changes from baseline for A1C over time and at endpoint are shown in Figure 1. The proportion of patients who discontinued for lack of glycemic control or who were rescued for meeting prespecified glycemic criteria was 15% in the ONGLYZA 2.5 mg add-on to metformin group, 13% in the ONGLYZA 5 mg add-on to metformin group, and 27% in the placebo add-on to metformin group.

Table 5: Glycemic Parameters at Week 24 in a Placebo-Controlled Trial of ONGLYZA as Add-On Combination Therapy with Metformin HCl [Intent-to-treat population using last observation on trial or last observation prior to pioglitazone rescue therapy for patients needing rescue.]
Efficacy Parameter | ONGLYZA 2.5 mg + Metformin HCl N=192 | ONGLYZA 5 mg + Metformin HCl N=191 | Placebo + Metformin HCl N=179
Hemoglobin A1C (%) | N=186 | N=186 | N=175
Baseline (mean) | 8.1 | 8.1 | 8.1
Change from baseline (adjusted mean [Least squares mean adjusted for baseline value.]) | −0.6 | −0.7 | +0.1
Difference from placebo (adjusted mean) | −0.7 [p-value <0.0001 compared to placebo + metformin HCl.] | −0.8
95% Confidence Interval | (−0.9, −0.5) | (−1.0, −0.6)
Percent of patients achieving A1C <7% | 37% [p-value <0.05 compared to placebo + metformin HCl.] (69/186) | 44% (81/186) | 17% (29/175)
Fasting Plasma Glucose (mg/dL) | N=188 | N=187 | N=176
Baseline (mean) | 174 | 179 | 175
Change from baseline (adjusted mean) | −14 | −22 | +1
Difference from placebo (adjusted mean) | −16 | −23
95% Confidence Interval | (−23, −9) | (−30, −16)
2-hour Postprandial Glucose (mg/dL) | N=155 | N=155 | N=135
Baseline (mean) | 294 | 296 | 295
Change from baseline (adjusted mean) | −62 | −58 | −18
Difference from placebo (adjusted mean) | −44 | −40
95% Confidence Interval | (−60, −27) | (−56, −24)

Figure 1: Mean Change from Baseline in A1C in a Placebo-Controlled Trial of ONGLYZA as Add-On Combination Therapy with Metformin HCl*

*Includes patients with a baseline and week 24 value.
Week 24 (LOCF) includes intent-to-treat population using last observation on trial prior to pioglitazone rescue therapy for patients needing rescue. Mean change from baseline is adjusted for baseline value.

Add-On Combination Therapy with a Thiazolidinedione

A total of 565 patients with type 2 diabetes mellitus participated in this 24-week, randomized, double-blind, placebo-controlled trial to evaluate the efficacy and safety of ONGLYZA in combination with a thiazolidinedione (TZD) in patients with inadequate glycemic control (A1C ≥7% to ≤10.5%) on TZD alone. To qualify for enrollment, patients were required to be on a stable dose of pioglitazone (30-45 mg once daily) or rosiglitazone (4 mg once daily or 8 mg either once daily or in two divided doses of 4 mg) for at least 12 weeks.

Patients who met eligibility criteria were enrolled in a single-blind, 2-week, dietary and exercise placebo lead-in period during which patients received TZD at their pre-trial dose. Following the lead-in period, eligible patients were randomized to 2.5 mg or 5 mg of ONGLYZA or placebo in addition to their current dose of TZD. Patients who failed to meet specific glycemic goals during the trial were treated with metformin HCl rescue, added on to existing trial medications. Dose titration of ONGLYZA or TZD was not permitted during the trial. A change in TZD regimen from rosiglitazone to pioglitazone at specified, equivalent therapeutic doses was permitted at the investigator’s discretion if believed to be medically appropriate.

ONGLYZA 2.5 mg and 5 mg add-on to TZD provided significant improvements in A1C, FPG, and PPG compared with placebo add-on to TZD (Table 6). The proportion of patients who discontinued for lack of glycemic control or who were rescued for meeting prespecified glycemic criteria was 10% in the ONGLYZA 2.5 mg add-on to TZD group, 6% for the ONGLYZA 5 mg add-on to TZD group, and 10% in the placebo add-on to TZD group.

Table 6: Glycemic Parameters at Week 24 in a Placebo-Controlled Trial of ONGLYZA as Add-On Combination Therapy with a Thiazolidinedione [Intent-to-treat population using last observation on trial or last observation prior to metformin HCl rescue therapy for patients needing rescue]
Efficacy Parameter | ONGLYZA 2.5 mg + TZD N=195 | ONGLYZA 5 mg + TZD N=186 | Placebo + TZD N=184
Hemoglobin A1C (%) | N=192 | N=183 | N=180
Baseline (mean) | 8.3 | 8.4 | 8.2
Change from baseline (adjusted mean [Least squares mean adjusted for baseline value]) | −0.7 | −0.9 | −0.3
Difference from placebo (adjusted mean) | −0.4 [p-value <0.0001 compared to placebo + TZD] | −0.6 [p-value <0.05 compared to placebo + TZD]
95% Confidence Interval | (−0.6, −0.2) | (−0.8, −0.4)
Percent of patients achieving A1C <7% | 42% (81/192) | 42% (77/184) | 26% (46/180)
Fasting Plasma Glucose (mg/dL) | N=193 | N=185 | N=181
Baseline (mean) | 163 | 160 | 162
Change from baseline (adjusted mean) | −14 | −17 | −3
Difference from placebo (adjusted mean) | −12 | −15
95% Confidence Interval | (−20, −3) | (−23, −6)
2-hour Postprandial Glucose (mg/dL) | N=156 | N=134 | N=127
Baseline (mean) | 296 | 303 | 291
Change from baseline (adjusted mean) | −55 | −65 | −15
Difference from placebo (adjusted mean) | −40 | −50
95% Confidence Interval | (−56, −24) | (−66, −34)

Add-On Combination Therapy with Glyburide

A total of 768 patients with type 2 diabetes mellitus participated in this 24-week, randomized, double-blind, placebo-controlled trial to evaluate the efficacy and safety of ONGLYZA in combination with a sulfonylurea (SU) in patients with inadequate glycemic control at enrollment (A1C ≥7.5% to ≤10%) on a submaximal dose of SU alone. To qualify for enrollment, patients were required to be on a submaximal dose of SU for 2 months or greater. In this trial, ONGLYZA in combination with a fixed, intermediate dose of SU was compared to titration to a higher dose of SU.

Patients who met eligibility criteria were enrolled in a single-blind, 4-week, dietary and exercise lead-in period, and placed on glyburide 7.5 mg once daily. Following the lead-in period, eligible patients with A1C ≥7% to ≤10% were randomized to either 2.5 mg or 5 mg of ONGLYZA add-on to 7.5 mg glyburide or to placebo plus a 10 mg total daily dose of glyburide. Patients who received placebo were eligible to have glyburide up-titrated to a total daily dose of 15 mg. Up-titration of glyburide was not permitted in patients who received ONGLYZA 2.5 mg or 5 mg. Glyburide could be down-titrated in any treatment group once during the 24-week trial period due to hypoglycemia as deemed necessary by the investigator. Approximately 92% of patients in the placebo plus glyburide group were up-titrated to a final total daily dose of 15 mg during the first 4 weeks of the trial period. Patients who failed to meet specific glycemic goals during the trial were treated with metformin HCl rescue, added on to existing trial medication. Dose titration of ONGLYZA was not permitted during the trial.

In combination with glyburide, ONGLYZA 2.5 mg and 5 mg provided significant improvements in A1C, FPG, and PPG compared with the placebo plus up-titrated glyburide group (Table 7). The proportion of patients who discontinued for lack of glycemic control or who were rescued for meeting prespecified glycemic criteria was 18% in the ONGLYZA 2.5 mg add-on to glyburide group, 17% in the ONGLYZA 5 mg add-on to glyburide group, and 30% in the placebo plus up-titrated glyburide group.

Table 7: Glycemic Parameters at Week 24 in a Placebo-Controlled Trial of ONGLYZA as Add-On Combination Therapy with Glyburide [Intent-to-treat population using last observation on trial or last observation prior to metformin HCl rescue therapy for patients needing rescue.]
Efficacy Parameter | ONGLYZA 2.5 mg + Glyburide 7.5 mg N=248 | ONGLYZA 5 mg + Glyburide 7.5 mg N=253 | Placebo + Up-Titrated Glyburide N=267
Hemoglobin A1C (%) | N=246 | N=250 | N=264
Baseline (mean) | 8.4 | 8.5 | 8.4
Change from baseline (adjusted mean [Least squares mean adjusted for baseline value.]) | −0.5 | −0.6 | +0.1
Difference from up-titrated glyburide (adjusted mean) | −0.6 [p-value <0.0001 compared to placebo + up-titrated glyburide.] | −0.7
95% Confidence Interval | (−0.8, −0.5) | (−0.9, −0.6)
Percent of patients achieving A1C <7% | 22% [p-value <0.05 compared to placebo + up-titrated glyburide.] (55/246) | 23% (57/250) | 9% (24/264)
Fasting Plasma Glucose (mg/dL) | N=247 | N=252 | N=265
Baseline (mean) | 170 | 175 | 174
Change from baseline (adjusted mean) | −7 | −10 | +1
Difference from up-titrated glyburide (adjusted mean) | −8 | −10
95% Confidence Interval | (−14, −1) | (−17, −4)
2-hour Postprandial Glucose (mg/dL) | N=195 | N=202 | N=206
Baseline (mean) | 309 | 315 | 323
Change from baseline (adjusted mean) | −31 | −34 | +8
Difference from up-titrated glyburide (adjusted mean) | −38 | −42
95% Confidence Interval | (−50, −27) | (−53, −31)

Coadministration with Metformin HCl in Treatment-Naive Patients

A total of 1306 treatment-naive patients with type 2 diabetes mellitus participated in this 24-week, randomized, double-blind, active-controlled trial to evaluate the efficacy and safety of ONGLYZA coadministered with metformin HCl in patients with inadequate glycemic control (A1C ≥8% to ≤12%) on diet and exercise alone. Patients were required to be treatment-naive to be enrolled in this trial.

Patients who met eligibility criteria were enrolled in a single-blind, 1-week, dietary and exercise placebo lead-in period. Patients were randomized to one of four treatment arms: ONGLYZA 5 mg + metformin HCl 500 mg, saxagliptin 10 mg + metformin HCl 500 mg, saxagliptin 10 mg + placebo, or metformin HCl 500 mg + placebo. The 10 mg saxagliptin dosage is not an approved dosage. ONGLYZA was dosed once daily. In the 3 treatment groups using metformin HCl, the metformin HCl dose was up-titrated weekly in 500 mg per day increments, as tolerated, to a maximum of 2,000 mg per day based on FPG. Patients who failed to meet specific glycemic goals during the studies were treated with pioglitazone rescue as add-on therapy.

Coadministration of ONGLYZA 5 mg plus metformin HCl provided significant improvements in A1C, FPG, and PPG compared with placebo plus metformin (Table 8).

Table 8: Glycemic Parameters at Week 24 in a Placebo-Controlled Trial of ONGLYZA Coadministration with Metformin HCl in Treatment-Naive Patients [Intent-to-treat population using last observation on trial or last observation prior to pioglitazone rescue therapy for patients needing rescue.]
Efficacy Parameter | ONGLYZA 5 mg + Metformin HCl N=320 | Placebo + Metformin HCl N=328
Hemoglobin A1C (%) | N=306 | N=313
Baseline (mean) | 9.4 | 9.4
Change from baseline (adjusted mean [Least squares mean adjusted for baseline value.]) | −2.5 | −2.0
Difference from placebo + metformin HCl (adjusted mean) | −0.5 [p-value <0.0001 compared to placebo + metformin HCl.]
95% Confidence Interval | (−0.7, −0.4)
Percent of patients achieving A1C <7% | 60% [p-value <0.05 compared to placebo + metformin HCl.] (185/307) | 41% (129/314)
Fasting Plasma Glucose (mg/dL) | N=315 | N=320
Baseline (mean) | 199 | 199
Change from baseline (adjusted mean) | −60 | −47
Difference from placebo + metformin HCl (adjusted mean) | −13
95% Confidence Interval | (−19, −6)
2-hour Postprandial Glucose (mg/dL) | N=146 | N=141
Baseline (mean) | 340 | 355
Change from baseline (adjusted mean) | −138 | −97
Difference from placebo + metformin HCl (adjusted mean) | −41
95% Confidence Interval | (−57, −25)

Add-On Combination Therapy with Metformin HCl versus Glipizide Add-On Combination Therapy with Metformin HCl

In this 52-week, active-controlled trial, a total of 858 patients with type 2 diabetes mellitus and inadequate glycemic control (A1C >6.5% and ≤10%) on metformin HCl alone were randomized to double-blind add-on therapy with ONGLYZA or glipizide. Patients were required to be on a stable dose of metformin HCl (at least 1,500 mg daily) for at least 8 weeks prior to enrollment.

Patients who met eligibility criteria were enrolled in a single-blind, 2-week, dietary and exercise placebo lead-in period during which patients received metformin HCl (1,500-3,000 mg based on their pre-trial dose). Following the lead-in period, eligible patients were randomized to 5 mg of ONGLYZA or 5 mg of glipizide in addition to their current dose of open-label metformin HCl. Patients in the glipizide plus metformin HCl group underwent blinded titration of the glipizide dose during the first 18 weeks of the trial up to a maximum glipizide dose of 20 mg per day. Titration was based on a goal FPG ≤110 mg/dL or the highest tolerable glipizide dose. Fifty percent (50%) of the glipizide-treated patients were titrated to the 20-mg daily dose; 21% of the glipizide-treated patients had a final daily glipizide dose of 5 mg or less. The mean final daily dose of glipizide was 15 mg.

After 52 weeks of treatment, ONGLYZA and glipizide resulted in similar mean reductions from baseline in A1C when added to metformin HCl therapy (Table 9). This conclusion may be limited to patients with baseline A1C comparable to those in the trial (91% of patients had baseline A1C <9%).

From a baseline mean body weight of 89 kg, there was a statistically significant mean reduction of 1.1 kg in patients treated with ONGLYZA compared to a mean weight gain of 1.1 kg in patients treated with glipizide (p<0.0001).

Table 9: Glycemic Parameters at Week 52 in an Active-Controlled Trial of ONGLYZA versus Glipizide in Combination with Metformin HCl [Intent-to-treat population using last observation on trial.]
Efficacy Parameter | ONGLYZA 5 mg + Metformin HCl N=428 | Titrated Glipizide + Metformin HCl N=430
Hemoglobin A1C (%) | N=423 | N=423
Baseline (mean) | 7.7 | 7.6
Change from baseline (adjusted mean [Least squares mean adjusted for baseline value.]) | −0.6 | −0.7
Difference from glipizide + metformin HCl (adjusted mean) | 0.1
95% Confidence Interval | (−0.02, 0.2) [ONGLYZA + metformin HCl is considered non-inferior to glipizide + metformin HCl because the upper limit of this confidence interval is less than the prespecified non-inferiority margin of 0.35%.]
Fasting Plasma Glucose (mg/dL) | N=420 | N=420
Baseline (mean) | 162 | 161
Change from baseline (adjusted mean) | −9 | −16
Difference from glipizide + metformin HCl (adjusted mean) | 6
95% Confidence Interval | (2, 11) [Significance not tested.]

Add-On Combination Therapy with Insulin (with or without metformin HCl)

A total of 455 patients with type 2 diabetes mellitus participated in this 24-week, randomized, double-blind, placebo-controlled trial to evaluate the efficacy and safety of ONGLYZA in combination with insulin in patients with inadequate glycemic control (A1C ≥7.5% and ≤11%) on insulin alone (N=141) or on insulin in combination with a stable dose of metformin HCl (N=314). Patients were required to be on a stable dose of insulin (≥30 units to ≤150 units daily) with ≤20% variation in total daily dose for ≥8 weeks prior to screening. Patients entered the trial on intermediate- or long-acting (basal) insulin or premixed insulin. Patients using short-acting insulins were excluded unless the short-acting insulin was administered as part of a premixed insulin.

Patients who met eligibility criteria were enrolled in a single-blind, four-week, dietary and exercise placebo lead-in period during which patients received insulin (and metformin HCl if applicable) at their pretrial dose(s). Following the lead-in period, eligible patients were randomized to add-on therapy with either ONGLYZA 5 mg or placebo. Doses of the antidiabetic therapies were to remain stable but patients were rescued and allowed to adjust the insulin regimen if specific glycemic goals were not met or if the investigator learned that the patient had self-increased the insulin dose by >20%. Data after rescue were excluded from the primary efficacy analyses.

Add-on therapy with ONGLYZA 5 mg provided significant improvements from baseline to Week 24 in A1C and PPG compared with add-on placebo (Table 10). Similar mean reductions in A1C versus placebo were observed for patients using ONGLYZA 5 mg add-on to insulin alone and ONGLYZA 5 mg add-on to insulin in combination with metformin HCl (−0.4% and −0.4%, respectively). The percentage of patients who discontinued for lack of glycemic control or who were rescued was 23% in the ONGLYZA group and 32% in the placebo group.

The mean daily insulin dose at baseline was 53 units in patients treated with ONGLYZA 5 mg and 55 units in patients treated with placebo. The mean change from baseline in daily dose of insulin was 2 units for the ONGLYZA 5 mg group and 5 units for the placebo group.

Table 10: Glycemic Parameters at Week 24 in a Placebo-Controlled Trial of ONGLYZA as Add-On Combination Therapy with Insulin [Intent-to-treat population using last observation on trial or last observation prior to insulin rescue therapy for patients needing rescue.]
Efficacy Parameter | ONGLYZA 5 mg + Insulin (+/− Metformin HCl) N=304 | Placebo + Insulin (+/− Metformin HCl) N=151
Hemoglobin A1C (%) | N=300 | N=149
Baseline (mean) | 8.7 | 8.7
Change from baseline (adjusted mean [Least squares mean adjusted for baseline value and metformin HCl use at baseline.]) | −0.7 | −0.3
Difference from placebo (adjusted mean) | −0.4 [p-value <0.0001 compared to placebo + insulin.]
95% Confidence Interval | (−0.6, −0.2)
2-hour Postprandial Glucose (mg/dL) | N=262 | N=129
Baseline (mean) | 251 | 255
Change from baseline (adjusted mean) | −27 | −4
Difference from placebo (adjusted mean) | −23 [p-value <0.05 compared to placebo + insulin.]
95% Confidence Interval | (−37, −9)

The change in fasting plasma glucose from baseline to Week 24 was also tested, but was not statistically significant. The percent of patients achieving an A1C <7% was 17% (52/300) with ONGLYZA in combination with insulin compared to 7% (10/149) with placebo. Significance was not tested.

Add-On Combination Therapy with Metformin HCl plus Sulfonylurea

A total of 257 patients with type 2 diabetes mellitus participated in this 24-week, randomized, double-blind, placebo-controlled trial to evaluate the efficacy and safety of ONGLYZA in combination with metformin HCl plus a sulfonylurea in patients with inadequate glycemic control (A1C ≥7% and ≤10%). Patients were to be on a stable combined dose of metformin HCl extended-release or immediate-release (at maximum tolerated dose, with minimum dose for enrollment being 1,500 mg) and a sulfonylurea (at maximum tolerated dose, with minimum dose for enrollment being ≥50% of the maximum recommended dose) for ≥8 weeks prior to enrollment.

Patients who met eligibility criteria were entered in a 2-week enrollment period to allow assessment of inclusion/exclusion criteria. Following the 2-week enrollment period, eligible patients were randomized to either double-blind ONGLYZA (5 mg once daily) or double-blind matching placebo for 24 weeks. During the 24-week double-blind treatment period, patients were to receive metformin HCl and a sulfonylurea at the same constant dose ascertained during enrollment. Sulfonylurea dose could be down titrated once in the case of a major hypoglycemic event or recurring minor hypoglycemic events. In the absence of hypoglycemia, titration (up or down) of trial medication during the treatment period was prohibited.

ONGLYZA in combination with metformin HCl plus a sulfonylurea provided significant improvements in A1C and PPG compared with placebo in combination with metformin HCl plus a sulfonylurea (Table 11). The percentage of patients who discontinued for lack of glycemic control was 6% in the ONGLYZA group and 5% in the placebo group.

Table 11: Glycemic Parameters at Week 24 in a Placebo-Controlled Trial of ONGLYZA as Add-On Combination Therapy with Metformin HCl plus Sulfonylurea [Intent-to-treat population using last observation prior to discontinuation]
Efficacy Parameter | ONGLYZA 5 mg + Metformin HCl plus Sulfonylurea N=129 | Placebo + Metformin HCl plus Sulfonylurea N=128
Hemoglobin A1C (%) | N=127 | N=127
Baseline (mean) | 8.4 | 8.2
Change from baseline (adjusted mean [Least squares mean adjusted for baseline value]) | −0.7 | −0.1
Difference from placebo (adjusted mean) | −0.7 [p-value <0.0001 compared to placebo + metformin HCl plus sulfonylurea]
95% Confidence Interval | (−0.9, −0.5)
2-hour Postprandial Glucose (mg/dL) | N=115 | N=113
Baseline (mean) | 268 | 262
Change from baseline (adjusted mean) | −12 | 5
Difference from placebo (adjusted mean) | −17 [p-value <0.05 compared to placebo + metformin HCl plus sulfonylurea]
95% Confidence Interval | (−32, −2)

The change in fasting plasma glucose from baseline to Week 24 was also tested, but was not statistically significant. The percent of patients achieving an A1C <7% was 31% (39/127) with ONGLYZA in combination with metformin HCl plus a sulfonylurea compared to 9% (12/127) with placebo. Significance was not tested.

Add-on Combination Therapy with Metformin HCl plus an SGLT2 Inhibitor

A total of 315 patients with type 2 diabetes mellitus participated in this 24-week randomized, double-blind, placebo-controlled trial to evaluate the efficacy and safety of ONGLYZA added to dapagliflozin (an SGLT2 inhibitor) and metformin HCl in patients with a baseline of HbA1c ≥7% to ≤10.5%. The mean age of these patients was 54.6 years, 1.6% were 75 years or older and 52.7% were female. The population was 87.9% White, 6.3% Black or African American, 4.1% Asian, and 1.6% other races. At baseline the population had diabetes mellitus for an average of 7.7 years and a mean HbA1c of 7.9%. The mean eGFR at baseline was 93.4 mL/min/1.73 m2. Patients were required to be on a stable dose of metformin HCl (≥1,500 mg per day) for at least 8 weeks prior to enrollment. Eligible patients who completed the screening period entered the lead in treatment period, which included open-label metformin HCl and 10 mg dapagliflozin treatment. Following the lead-in period, eligible patients were randomized to ONGLYZA 5 mg (N=153) or placebo (N =162).

The group treated with add-on ONGLYZA had statistically significant greater reductions in HbA1c from baseline versus the group treated with placebo (see Table 12).

Table 12: HbA1c Change from Baseline at Week 24 in a Placebo-Controlled Trial of ONGLYZA as Add-on to Dapagliflozin and Metformin HCl [There were 6.5% (n=10) of randomized patients in the saxagliptin arm and 3.1% (n=5) in the placebo arm for whom change from baseline HbA1c data was missing at week 24. Of the patients who discontinued trial medication early, 9.1% (1 of 11) in the saxagliptin arm and 16.7% (1 of 6) in the placebo arm had HbA1c measured at week 24.]
 | ONGLYZA 5 mg; (N=153) [Number of randomized and treated patients.] | Placebo; (N=162)
 | In combination with Dapagliflozin and Metformin HCl
Hemoglobin A1C (%) [Analysis of Covariance including all post-baseline data regardless of rescue or treatment discontinuation. Model estimates calculated using multiple imputation to model washout of the treatment effect using placebo data for all patients having missing Week 24 data.]
Baseline (mean) | 8.0 | 7.9
Change from baseline (adjusted mean [Least squares mean adjusted for baseline value.]); 95% Confidence Interval | −0.5; (−0.6, −0.4) | −0.2; (−0.3, −0.1)
Difference from placebo (adjusted mean); 95% Confidence Interval | −0.4 [p-value <0.0001]; (−0.5, −0.2)

The known proportion of patients achieving HbA1c <7% at Week 24 was 35.3% in the saxagliptin treated group compared to 23.1% in the placebo treated group.

14.2 Renal Impairment

A total of 170 patients participated in a 12-week, randomized, double-blind, placebo-controlled trial conducted to evaluate the efficacy and safety of ONGLYZA 2.5 mg once daily compared with placebo in patients with type 2 diabetes mellitus and moderate (n=90) or severe (n=41) renal impairment or ESRD (n=39). In this trial, 98% of the patients were using background antidiabetic medications (75% were using insulin and 31% were using oral antidiabetic medications, mostly sulfonylureas).

After 12 weeks of treatment, ONGLYZA 2.5 mg provided significant improvement in A1C compared to placebo (Table 13). In the subgroup of patients with ESRD, ONGLYZA and placebo resulted in comparable reductions in A1C from baseline to Week 12. This finding is inconclusive because the trial was not adequately powered to show efficacy within specific subgroups of renal impairment.

After 12 weeks of treatment, the mean change in FPG was −12 mg/dL with ONGLYZA 2.5 mg and −13 mg/dL with placebo. Compared to placebo, the mean change in FPG with ONGLYZA was −12 mg/dL in the subgroup of patients with moderate renal impairment, −4 mg/dL in the subgroup of patients with severe renal impairment, and +44 mg/dL in the subgroup of patients with ESRD. These findings are inconclusive because the trial was not adequately powered to show efficacy within specific subgroups of renal impairment.

Table 13: A1C at Week 12 in a Placebo-Controlled Trial of ONGLYZA in Patients with Renal Impairment [Intent-to-treat population using last observation on trial.]
Efficacy Parameter | ONGLYZA 2.5 mg N=85 | Placebo N=85
Hemoglobin A1C (%) | N=81 | N=83
Baseline (mean) | 8.4 | 8.1
Change from baseline (adjusted mean [Least squares mean adjusted for baseline value.]) | −0.9 | −0.4
Difference from placebo (adjusted mean) | −0.4 [p-value <0.01 compared to placebo.]
95% Confidence Interval | (−0.7, −0.1)

14.3 Cardiovascular Safety Trial

The cardiovascular risk of ONGLYZA was evaluated in SAVOR, a multicenter, multinational, randomized, double-blind trial comparing ONGLYZA (N=8280) to placebo (N=8212), both administered in combination with standard of care, in adult patients with type 2 diabetes mellitus at high risk for atherosclerotic cardiovascular disease. Of the randomized trial patients, 97.5% completed the trial, and the median duration of follow-up was approximately 2 years. The trial was event-driven, and patients were followed until a sufficient number of events were accrued.

Patients were at least 40 years of age, had A1C ≥6.5%, and multiple risk factors (21% of randomized patients) for cardiovascular disease (age ≥55 years for men and ≥60 years for women plus at least one additional risk factor of dyslipidemia, hypertension, or current cigarette smoking) or established (79% of the randomized patients) cardiovascular disease defined as a history of ischemic heart disease, peripheral vascular disease, or ischemic stroke. Overall, the use of diabetes medications was balanced across treatment groups (metformin HCl 69%, insulin 41%, sulfonylureas 40%, and TZDs 6%). The use of cardiovascular disease medications was also balanced (angiotensin-converting enzyme (ACE) inhibitors or angiotensin receptor blockers (ARBs) 79%, statins 78%, aspirin 75%, beta-blockers 62%, and non-aspirin antiplatelet medications 24%).

The majority of patients were male (67%) and White (75%) with a mean age of 65 years. Approximately 16% of the population had moderate (estimated glomerular filtration rate [eGFR] ≥30 to ≤50 mL/min/1.73 m^2) to severe (eGFR <30 mL/min/1.73 m^2) renal impairment, and 13% had a prior history of heart failure. Patients had a median duration of type 2 diabetes mellitus of approximately 10 years, and a mean baseline A1C level of 8.0%. Approximately 5% of patients were treated with diet and exercise only at baseline. Overall, the use of diabetes medications was balanced across treatment groups (metformin HCl 69%, insulin 41%, sulfonylureas 40%, and TZDs 6%). The use of cardiovascular disease medications was also balanced (ACE inhibitors or ARBs 79%, statins 78%, aspirin 75%, beta-blockers 62%, and non-aspirin antiplatelet medications 24%).

The primary analysis in SAVOR was time to first occurrence of a Major Adverse Cardiac Event (MACE). A major adverse cardiac event in SAVOR was defined as a cardiovascular death or a nonfatal myocardial infarction (MI) or a nonfatal ischemic stroke. The trial was designed as a non-inferiority trial with a pre-specified risk margin of 1.3 for the hazard ratio of MACE and was also powered for a superiority comparison if non-inferiority was demonstrated.

The results of SAVOR, including the contribution of each component to the primary composite endpoint, are shown in Table 14. The incidence rate of MACE was similar in both treatment arms: 3.8 MACE per 100 patient-years on placebo vs. 3.8 MACE per 100 patient-years on ONGLYZA. The estimated hazard ratio of MACE associated with ONGLYZA relative to placebo was 1.00 with a 95.1% confidence interval of (0.89, 1.12). The upper bound of this confidence interval, 1.12, excluded a risk margin larger than 1.3.

Table 14: Major Adverse Cardiovascular Events (MACE) by Treatment Group in the SAVOR Trial
 | ONGLYZA |  | Placebo |  | Hazard Ratio
 | Number of Patients (%) | Rate per 100 PY | Number of Patients (%) | Rate per 100 PY | (95.1% CI)
Composite of first event of CV death, non-fatal MI or non-fatal ischemic stroke (MACE) | N=8280 | Total PY = 16308.8 | N=8212 | Total PY = 16156.0
Composite of first event of CV death, non-fatal MI or non-fatal ischemic stroke (MACE) | 613 (7.4) | 3.8 | 609 (7.4) | 3.8 | 1.00 (0.89, 1.12)
CV death | 245 (3.0) | 1.5 | 234 (2.8) | 1.4
Non-fatal MI | 233 (2.8) | 1.4 | 260 (3.2) | 1.6
Non-fatal ischemic stroke | 135 (1.6) | 0.8 | 115 (1.4) | 0.7

The Kaplan-Meier-based cumulative event probability is presented in Figure 2 for time to first occurrence of the primary MACE composite endpoint by treatment arm. The curves for both ONGLYZA and placebo arms are close together throughout the duration of the trial. The estimated cumulative event probability is approximately linear for both arms, indicating that the incidence of MACE for both arms was constant over the trial duration.

Figure 2: Cumulative Percent of Time to First MACE

Vital status was obtained for 99% of patients in the trial. There were 798 deaths in the SAVOR trial. Numerically more patients (5.1%) died in the ONGLYZA group than in the placebo group (4.6%). The risk of deaths from all cause (Table 15) was not statistically different between the treatment groups (HR: 1.11; 95.1% CI: 0.96, 1.27).

Table 15: All-cause mortality by Treatment Group in the SAVOR Trial
 | ONGLYZA |  | Placebo |  | Hazard Ratio
 | Number of Patients (%) | Rate per 100 PY | Number of Patients (%) | Rate per 100 PY | (95.1% CI)
 | N=8280 | PY=16645.3 | N=8212 | PY=16531.5
All-cause mortality | 420 (5.1) | 2.5 | 378 (4.6) | 2.3 | 1.11 (0.96, 1.27)
CV death | 269 (3.2) | 1.6 | 260 (3.2) | 1.6
Non-CV death | 151 (1.8) | 0.9 | 118 (1.4) | 0.7

16 HOW SUPPLIED/STORAGE AND HANDLING

How Supplied

ONGLYZA tablets have markings on both sides and are available in the strengths and packages listed in Table 16.

Table 16: ONGLYZA Tablet Presentations
Tablet Strength | Film-Coated Tablet Color/Shape | Tablet Markings | Package Size | NDC Code
5 mg | pink biconvex, round | “5” on one side and “4215” on the reverse, in blue ink | Bottles of 30 Bottles of 90 | 0310-6105-30 0310-6105-90
2.5 mg | pale yellow to light yellow biconvex, round | “2.5” on one side and “4214” on the reverse, in blue ink | Bottles of 30 Bottles of 90 | 0310-6100-30 0310-6100-90

STORAGE AND HANDLING

Storage and Handling

Store at 20°C-25°C (68°F-77°F); excursions permitted to 15°C-30°C (59°F-86°F) [see USP Controlled Room Temperature].

17 PATIENT COUNSELING INFORMATION

Advise the patient to read the FDA-approved patient labeling (Medication Guide).

Pancreatitis

Inform patients that acute pancreatitis has been reported during postmarketing use of ONGLYZA. Educate patients that persistent severe abdominal pain, sometimes radiating to the back, which may or may not be accompanied by vomiting, is the hallmark symptom of acute pancreatitis. Instruct patients to promptly discontinue ONGLYZA and contact their health care provider if persistent severe abdominal pain occurs [see Warnings and Precautions (5.1)].

Heart Failure

Inform patients of the signs and symptoms of heart failure. Before initiating ONGLYZA, ask patients if they have a history of heart failure or other risk factors for heart failure including moderate to severe renal impairment. Instruct patients to contact their health care provider as soon as possible if they experience symptoms of heart failure, including increasing shortness of breath, rapid increase in weight or swelling of the feet [see Warnings and Precautions (5.2)].

Hypoglycemia with Concomitant Use with Insulin or Insulin Secretagogues

Inform patients that hypoglycemia can occur, particularly when insulin or an insulin secretagogue is used in combination with ONGLYZA. Educate patients about the risks, symptoms and appropriate management of hypoglycemia [see Warnings and Precautions (5.3)].

Hypersensitivity Reactions

Patients should be informed that serious allergic (hypersensitivity) reactions, such as angioedema, anaphylaxis, and exfoliative skin conditions, have been reported during postmarketing use of ONGLYZA. If symptoms of these allergic reactions (such as rash, skin flaking or peeling, urticaria, swelling of the skin, or swelling of the face, lips, tongue, and throat that may cause difficulty in breathing or swallowing) occur, patients must stop taking ONGLYZA and seek medical advice promptly [see Warnings and Precautions (5.4)].

Severe and Disabling Arthralgia

Inform patients that severe and disabling joint pain may occur with this class of drugs. The time to onset of symptoms can range from one day to years. Instruct patients to seek medical advice if severe joint pain occurs [see Warnings and Precautions (5.5)].

Bullous Pemphigoid

Inform patients that bullous pemphigoid may occur with this class of drugs. Instruct patients to seek medical advice if blisters or erosions occur [see Warnings and Precautions (5.6)].

Missed Dose

If a dose is missed, advise patients to take ONGLYZA as soon as they remember unless it is time for their next dose. Instruct patients not to take two doses of ONGLYZA at the same time.

Administration Instructions

Advise patients not to cut, crush, or chew ONGLYZA tablets.

ONGLYZA is a registered trademark of the AstraZeneca group of companies.

Distributed by:
AstraZeneca Pharmaceuticals LP
Wilmington, DE 19850

MEDICATION GUIDE

ONGLYZA® (on-GLY-zah)

(saxagliptin)

tablets, for oral use

What is the most important information I should know about ONGLYZA?

Serious side effects can happen to people taking ONGLYZA, including:

1) Inflammation of the pancreas (pancreatitis) which may be severe and lead to death.

Certain medical problems make you more likely to get pancreatitis.

Before you start taking ONGLYZA:

Tell your healthcare provider if you have ever had

- inflammation of your pancreas (pancreatitis)
- a history of alcoholism

- stones in your gallbladder (gallstones)
- high blood triglyceride levels

Stop taking ONGLYZA and contact your healthcare provider right away if you have pain in your stomach area (abdomen) that is severe and will not go away. The pain may be felt going from your abdomen through to your back. The pain may happen with or without vomiting. These may be symptoms of pancreatitis.

2) Heart failure. Heart failure means your heart does not pump blood well enough.

Before you start taking ONGLYZA:

Tell your healthcare provider if you

- have ever had heart failure or have problems with your kidneys.

Contact your healthcare provider right away if you have any of the following symptoms:

- increasing shortness of breath or trouble breathing, especially when you lie down
- swelling or fluid retention, especially in the feet, ankles or legs

- an unusually fast increase in weight
- unusual tiredness

These may be symptoms of heart failure.

What is ONGLYZA?

- ONGLYZA is a prescription medicine used along with diet and exercise to help control high blood sugar in adults with type 2 diabetes mellitus.
- ONGLYZA is not recommended for people with type 1 diabetes mellitus.
- ONGLYZA is not recommended for people with diabetic ketoacidosis (increased ketones in your blood or urine).

It is not known if ONGLYZA is safe and effective in children.

Who should not take ONGLYZA?

Do not take ONGLYZA if you:

- are allergic to any ingredients in ONGLYZA. See the end of this Medication Guide for a complete list of ingredients in ONGLYZA.
  Symptoms of a serious allergic reaction to ONGLYZA may include:

- swelling of your face, lips, throat, and other areas on your skin
- raised, red areas on your skin (hives)

- difficulty with swallowing or breathing
- skin rash, itching, flaking, or peeling

If you have these symptoms, stop taking ONGLYZA and contact your healthcare provider right away.

Before taking ONGLYZA, tell your healthcare provider about all of your medical conditions, including if you:

- have heart failure
- have or have had inflammation of your pancreas (pancreatitis)
- have kidney problems.
- are pregnant or plan to become pregnant. It is not known if ONGLYZA will harm your unborn baby. If you are pregnant, talk with your healthcare provider about the best way to control your blood sugar while you are pregnant.
- are breastfeeding or plan to breastfeed. ONGLYZA may be passed in your milk to your baby. Talk with your healthcare provider about the best way to feed your baby while you take ONGLYZA.

Tell your healthcare provider about all the medicines you take, including prescription and over-the-counter medicines, vitamins, and herbal supplements.

Know the medicines you take. Keep a list of your medicines and show it to your healthcare provider and pharmacist when you get a new medicine.

ONGLYZA may affect the way other medicines work, and other medicines may affect how ONGLYZA works. Contact your healthcare provider if you will be starting or stopping certain other types of medicines, such as antibiotics, or medicines that treat fungus or HIV/AIDS, because your dose of ONGLYZA might need to be changed.

How should I take ONGLYZA?

- Take ONGLYZA by mouth 1 time each day exactly as directed by your healthcare provider. Do not change your dose without talking to your healthcare provider.
- ONGLYZA can be taken with or without food.
- Do not cut, crush, or chew ONGLYZA tablets.
- Your healthcare provider should test your blood to measure how well your kidneys are working before and during your treatment with ONGLYZA. You may need a lower dose of ONGLYZA if your kidneys are not working well.
- If you miss a dose of ONGLYZA, Just take the next dose at your regular time. Do not take two doses at the same time.
- In case of an overdose contact the Poison Help line at 1-800-222-1222 or get medical help right away. Advice is also available online at poisonhelp.org.

What are the possible side effects of ONGLYZA?

ONGLYZA can cause serious side effects, including:

- See “What is the most important information I should know about ONGLYZA?”.
- Low blood sugar (hypoglycemia) If you take ONGLYZA with another medicine that can cause low blood sugar, such as a sulfonylurea or insulin, your risk of getting low blood sugar is higher. The dose of your sulfonylurea medicine
- or insulin may need to be lowered while you take ONGLYZA. Symptoms of low blood sugar include:
- shaking
- sweating
- rapid heartbeat
- change in vision
- hunger
- headache
- change in mood
- Allergic (hypersensitivity) reactions, such as:
- swelling of your face, lips, throat, and other areas on your skin
- difficulty with swallowing or breathing
- raised, red areas on your skin (hives)
- skin rash, itching, flaking, or peeling

If you have these symptoms, stop taking ONGLYZA and contact your healthcare provider right away.

- Joint pain. Some people who take medicines called DPP-4 inhibitors like ONGLYZA, may develop joint pain that can be severe. Call your healthcare provider if you have severe joint pain.
- Skin reaction. Some people who take medicines called DPP-4 inhibitors, like ONGLYZA, may develop a skin reaction called bullous pemphigoid that can require treatment in a hospital. Tell your healthcare provider right away if you develop blisters or the breakdown of the outer layer of your skin (erosion). Your healthcare provider may tell you to stop taking ONGLYZA.

The most common side effects of ONGLYZA include:

- upper respiratory tract infection
- urinary tract infection
- headache
- swelling or fluid retention in your hands, feet, or ankles (peripheral edema) may become worse in people who also take a thiazolidinedione to treat diabetes. If you do not know whether you are already on this type of medication, ask your healthcare provider.

These are not all of the possible side effects of ONGLYZA.

Call your doctor for medical advice about side effects. You may report side effects to FDA at 1-800-FDA-1088.

How should I store ONGLYZA?

Store ONGLYZA between 68°F to 77°F (20°C to 25°C).

Keep ONGLYZA and all medicines out of the reach of children.

General information about the use of ONGLYZA

Medicines are sometimes prescribed for purposes other than those listed in a Medication Guide. Do not use ONGLYZA for a condition for which it was not prescribed. Do not give ONGLYZA to other people, even if they have the same symptoms you have. It may harm them.

You can ask your healthcare provider for additional information about ONGLYZA that is written for health professionals.

What are the ingredients of ONGLYZA?

Active ingredient: saxagliptin

Inactive ingredients: croscarmellose sodium, lactose monohydrate, magnesium stearate, and microcrystalline cellulose. In addition, the film coating contains the following inactive ingredients: iron oxides, polyethylene glycol polyvinyl alcohol, talc, and titanium dioxide.

ONGLYZA is a registered trademark of the AstraZeneca group of companies. Distributed by: AstraZeneca Pharmaceuticals LP Wilmington, DE 19850. For more information, go to www.ONGLYZA.com or call 1 800 ONGLYZA.

This Medication Guide has been approved by the U.S. Food and Drug Administration. 10/2024

PACKAGE/LABEL PRINCIPAL DISPLAY PANEL – 5 mg

30 Tablets NDC 0310-6105-30
onglyza®
(saxagliptin) tablets
5 mg
DISPENSE WITH MEDICATION GUIDE
Rx only
AstraZeneca

PACKAGE/LABEL PRINCIPAL DISPLAY PANEL – 2.5 mg

30 Tablets NDC 0310-6100-30
onglyza®
(saxagliptin) tablets
2.5 mg
DISPENSE WITH MEDICATION GUIDE
Rx only
AstraZeneca